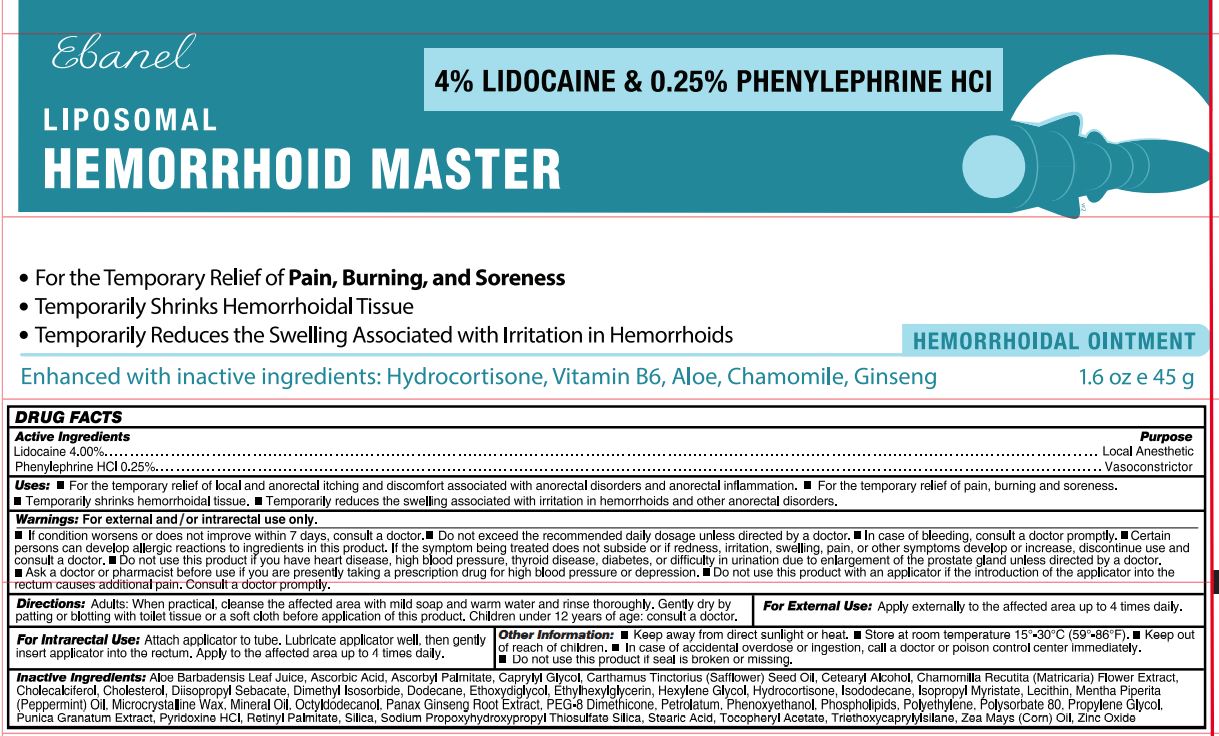 DRUG LABEL: Hemorrhoid Master
NDC: 72654-002 | Form: OINTMENT
Manufacturer: Ebanel Laboratories, Inc
Category: otc | Type: HUMAN OTC DRUG LABEL
Date: 20260209

ACTIVE INGREDIENTS: LIDOCAINE 40 mg/1 g; PHENYLEPHRINE 2.5 mg/1 g
INACTIVE INGREDIENTS: ALOE VERA LEAF; ASCORBIC ACID; ASCORBYL PALMITATE; CAPRYLYL GLYCOL; SAFFLOWER OIL; CETOSTEARYL ALCOHOL; CHAMOMILE; CHOLECALCIFEROL; CHOLESTEROL; DIISOPROPYL SEBACATE; DIMETHYL ISOSORBIDE; DODECANE; DIETHYLENE GLYCOL MONOETHYL ETHER; ETHYLHEXYLGLYCERIN; HEXYLENE GLYCOL; HYDROCORTISONE; ISODODECANE; ISOPROPYL MYRISTATE; PEPPERMINT OIL; MICROCRYSTALLINE WAX; MINERAL OIL; OCTYLDODECANOL; ASIAN GINSENG; PEG-8 DIMETHICONE; PETROLATUM; PHENOXYETHANOL; LECITHIN, SOYBEAN; HIGH DENSITY POLYETHYLENE; POLYSORBATE 80; PROPYLENE GLYCOL; PUNICA GRANATUM ROOT BARK; PYRIDOXINE HYDROCHLORIDE; VITAMIN A PALMITATE; SILICON DIOXIDE; SODIUM PROPOXYHYDROXYPROPYL THIOSULFATE SILICA; STEARIC ACID; .ALPHA.-TOCOPHEROL ACETATE; TRIETHOXYCAPRYLYLSILANE; CORN; ZINC OXIDE

Hemorrhoid Master

Active Ingredient

Lidocaine 4.00%

Phenylephrine HCl 0.25%

Purpose

Analgesic (Pain Relief)

(Vasoconstrictor)

Uses

- Helps relieve the anorectal itching and discomfort in the perianal area.
- Temporarily reduces swelling associated with irritation in hemorrhoids and other anorectal disorders.
- Temporarily shrinks hemorrhoidal tissue.

Warnings

For external and or intrarectal use only.

Stop use and ask a doctor

- If condition worsens or does not improve within 7 days.
- in case of bleeding.
- if allergic reaction to product occurs. If the symptoms being treated does not subside or if redness. irritation, swelling, pain, or other sympoms develop or increase.

When using this product

do not exceed the recommended daily dosage unless directed by a doctor.

Do not use

this product

- if you have heart disease, high blood pressure, thyroid disease, diabetes, or difficulty in urination due to enlargement of the prostate gland unless directed by a doctor.
- with an applicator if the introduction of the applicator into the rectum causes additional pain. Consult doctor promptly.

Ask a doctor before use

if you are

- presently taking a prescription drug for high blood pressure or depression.

Keep out of reach of children:

If swallowed, seek medical help or contact a Poison Control Center immediately.

Directions

Adults: Apply to the affected area up to 3 times dialy.

- Children under 12 years of age: consult a doctor.
- When practical, clean affected area with mild soap and warm water and rinse thoroughly. Gently dry (patting or blotting) with tissue or soft cloth before use.
- To use dispensing cap, attach it to tube, lubricate well, then gently insert part way into anus and squeeze tube to deliver medication. Thoroughly cleanse dispensing cap after use with mild soap and warm water and rinse thoroughly.

For Intrarectal Use:

Attach applicator to tube. Lubricate well, then gently insert applicator into the rectum.

For External use:Do not put this proudct into the rectum using fingers or any mechanical device.

Inactive Ingredients

Aloe Barbadensis Leaf Juice, Ascorbic Acid, Ascorbyl Palmitate, Caprylyl Glycol, Carthamus Tinctorius (Safflower) Seed Oil, Cetearyl Alcohol, Chamomilla Recutita (Matricaria) Flower Extract, Cholecalciferol, Cholesterol, Diisopropyl Sebacate, Dimethyl Isosorbide, Dodecane, Ethoxydiglycol, Ethylhexylglycerin, Hexylene Glycol, Hydrocortisone, Isododecane, Isopropyl Myristate, Lecithin, Mentha Piperita (Peppermint) Oil, Microcrystalline Wax, Mineral Oil, Octyldodecanol, Panax Ginseng Root Extract, PEG-8 Dimethicone, Petrolatum, Phenoxyethanol, Phospholipids, Polyethylene, Polysorbate 80, Propylene Glycol, Punica Granatum Extract, Pyridoxine HCl, Retinyl Palmitate, Silica, Sodium Propoxyhydroxypropyl Thiosulfate Silica, Stearic Acid, Tocopheryl Acetate, Triethoxycaprylylsilane, Zea Mays (Corn) Oil, Zinc Oxide.